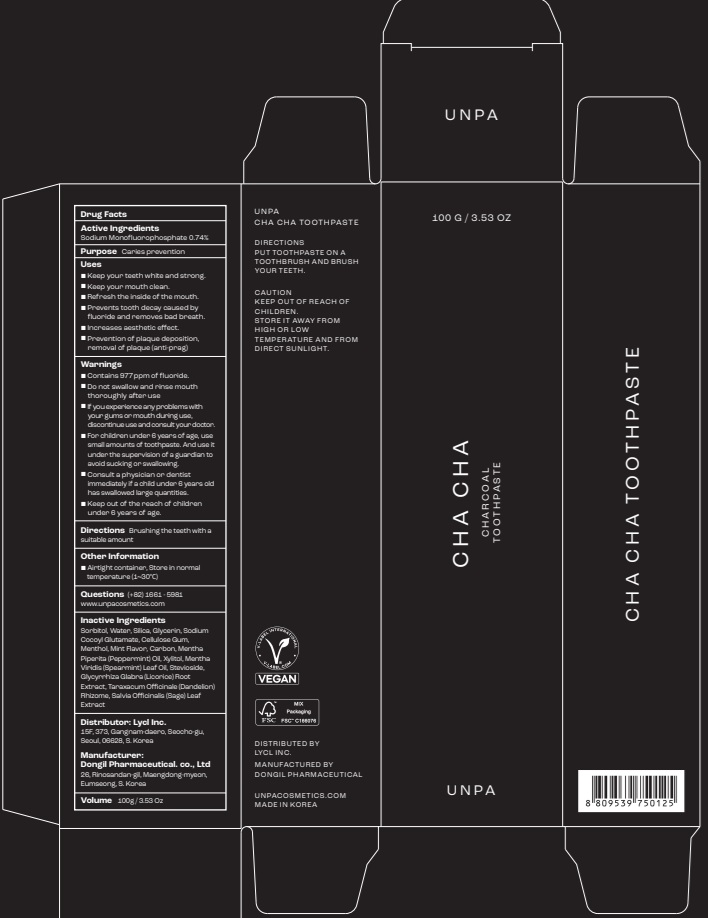 DRUG LABEL: unpa Cha Cha Toothpaste
NDC: 73134-010 | Form: PASTE, DENTIFRICE
Manufacturer: Lycl Inc.
Category: otc | Type: HUMAN OTC DRUG LABEL
Date: 20250925

ACTIVE INGREDIENTS: SODIUM MONOFLUOROPHOSPHATE 0.74 g/100 g
INACTIVE INGREDIENTS: SORBITOL; WATER; SILICON DIOXIDE

ACTIVE INGREDIENT

Sodium Monofluorophosphate 0.74%

INACTIVE INGREDIENTS

Sorbitol, Water, Silica, Glycerin, Sodium Cocoyl Glutamate, Cellulose Gum, Menthol, Mint Flavor, Carbon, Mentha Piperita (Peppermint) Oil, Xylitol, Mentha Viridis (Spearmint) Leaf Oil, Stevioside, Glycyrrhiza Glabra (Licorice) Root Extract, Taraxacum Officinale (Dandelion) Rhizome, Salvia Officinalis (Sage) Leaf Extract

PURPOSE

Caries prevention

WARNINGS

■ Contains 977ppm of fluoride.
■ Do not swallow and rinse mouth thoroughly after use
■ If you experience any problems with your gums or mouth during use, discontinue use and consult your doctor.
■ For children under 6 years of age, use small amounts of toothpaste. And use it under the supervision of a guardian to avoid sucking or swallowing.
■ Consult a physician or dentist immediately if a child under 6 years old has swallowed large quantities.
■ Keep out of the reach of children under 6 years of age.

KEEP OUT OF REACH OF CHILDREN

■ Keep out of the reach of children under 6 years of age.

Uses

■ Keep your teeth white and strong.
■ Keep your mouth clean.
■ Refresh the inside of the mouth.
■ Prevents tooth decay caused by fluoride and removes bad breath.
■ Increases aesthetic effect.
■ Prevention of plaque deposition, removal of plaque (anti-prag)

Directions

■ Brushing the teeth with a suitable amount

Other Information

■ Airtight container, Store in normal temperature (1~30℃)

Questions

(+82)1661 - 5981
www.unpacosmetics.com